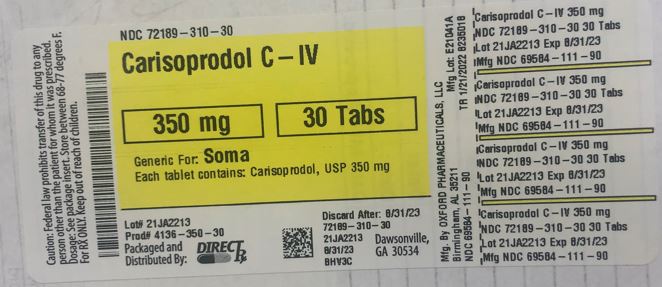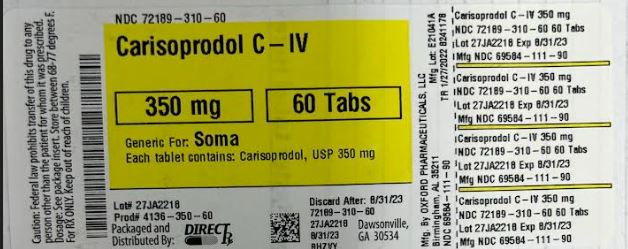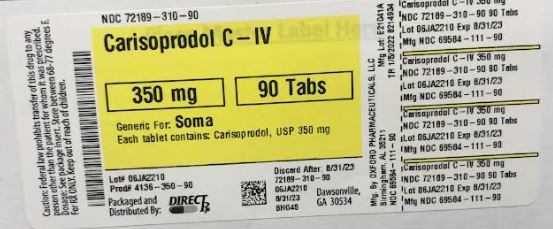 DRUG LABEL: CARISOPRODOL
NDC: 72189-310 | Form: TABLET
Manufacturer: Directrx
Category: prescription | Type: HUMAN PRESCRIPTION DRUG LABEL
Date: 20250121
DEA Schedule: CIV

ACTIVE INGREDIENTS: CARISOPRODOL 350 mg/1 1
INACTIVE INGREDIENTS: HYPROMELLOSE 2910 (50 MPA.S); STEARIC ACID; TALC; SODIUM STARCH GLYCOLATE TYPE A POTATO; MICROCRYSTALLINE CELLULOSE 101; LACTOSE MONOHYDRATE

CARISOPRODOL

INDICATIONS AND USAGE

Carisoprodol is indicated for the relief of discomfort associated with acute, painful musculoskeletal conditions in adults.

Limitation of Use
Carisoprodol should only be used for short periods (up to two or three weeks) because adequate evidence of effectiveness for more prolonged use has not been established and because acute, painful musculoskeletal conditions are generally of short duration. [see DOSAGE AND ADMINISTRATION (2)].

DOSAGE AND ADMINISTRATION

The recommended dose of carisoprodol is 350 mg three times a day and at bedtime.
The recommended maximum duration of carisoprodol use is up to two or three weeks.

DOSAGE FORMS AND STRENGTHS

350 mg Tablets: round, convex, white tablets, inscribed with 111 on one side and “O” on the other side.

CONTRAINDICATIONS

Carisoprodol is contraindicated in patients with a history of acute intermittent porphyria or a hypersensitivity reaction to a carbamate such as meprobamate.

WARNINGS AND PRECAUTIONS

5.1 Sedation

Carisoprodol has sedative properties (in the low back pain trials, 13% to 17% of patients who received carisoprodol experienced sedation compared to 6% of patients who received placebo) [see ADVERSE REACTIONS (6.1)] and may impair the mental and/or physical abilities required for the performance of potentially hazardous tasks such as driving a motor vehicle or operating machinery. There have been post-marketing reports of motor vehicle accidents associated with the use of carisoprodol.

Since the sedative effects of carisoprodol and other CNS depressants (e.g., alcohol, benzodiazepines, opioids, tricyclic antidepressants) may be additive, appropriate caution should be exercised with patients who take more than one of these CNS depressants simultaneously.

5.2 Abuse, Dependence, and Withdrawal

Carisoprodol, the active ingredient, has been subject to abuse, dependence, and withdrawal, misuse and criminal diversion. [see DRUG ABUSE AND DEPENDENCE (9.1, 9.2, 9.3)]. Abuse of carisoprodol poses a risk of overdosage which may lead to death, CNS and respiratory depression, hypotension, seizures and other disorders [see OVERDOSAGE (10)].

Post-marketing experience cases of carisoprodol abuse and dependence have been reported in patients with prolonged use and a history of drug abuse. Although most of these patients took other drugs of abuse, some patients solely abused carisoprodol. Withdrawal symptoms have been reported following abrupt cessation of carisoprodol after prolonged use. Reported withdrawal symptoms included insomnia, vomiting, abdominal cramps, headache, tremors, muscle twitching, ataxia, hallucinations, and psychosis. One of carisoprodol’s metabolites, meprobamate (a controlled substance), may also cause dependence [see CLINICAL PHARMACOLOGY (12.3)].

To reduce the risk of carisoprodol abuse assess the risk of abuse prior to prescribing. After prescribing, limit the length of treatment to three weeks for the relief of acute musculoskeletal discomfort, keep careful prescription records, monitor for signs of abuse and overdose, and educate patients and their families about abuse and on proper storage and disposal.

5.3 Seizures

There have been post-marketing reports of seizures in patients who received carisoprodol. Most of these cases have occurred in the setting of multiple drug overdoses (including drugs of abuse, illegal drugs, and alcohol) [see OVERDOSAGE (10)].

ADVERSE REACTIONS

6.1 Clinical Studies Experience

Because clinical studies are conducted under widely varying conditions, adverse reaction rates observed in clinical studies of a drug cannot be directly compared to rates in the clinical studies of another drug and may not reflect rates observed in practice.

The data described below are based on 1387 patients pooled from two double blind, randomized, multicenter, placebo controlled, one-week trials in adult patients with acute, mechanical, lower back pain [see CLINICAL STUDIES (14)]. In these studies, patients were treated with 250 mg of carisoprodol, 350 mg of carisoprodol, or placebo three times a day and at bedtime for seven days. The mean age was about 41 years old with 54% females and 46% males and 74 % Caucasian, 16 % Black, 9% Asian, and 2% other.

There were no deaths and there were no serious adverse reactions in these two trials. In these two studies, 2.7%, 2%, and 5.4%, of patients treated with placebo, 250 mg of carisoprodol, and 350 mg of carisoprodol, respectively, discontinued due to adverse events; and 0.5%, 0.5%, and 1.8% of patients treated with placebo, 250 mg of carisoprodol, and 350 mg of carisoprodol, respectively, discontinued due to central nervous system adverse reactions.

TABLE 1 displays adverse reactions reported with frequencies greater than 2% and more frequently than placebo in patients treated with carisoprodol in the two trials described above.

Table 1. Patients with Adverse Reactions in Controlled Studies
Adverse Reaction Placebo
(n=560)
n (%)

Carisoprodol 250 mg
(n=548)
n (%)

Carisoprodol 350 mg
(n=279)
n (%)
Drowsiness 31 (6)

73 (13)

47 (17)
Dizziness 11 (2) 43 (8) 19 (7)
Headache 11 (2) 26 (5) 9 (3)

6.2 Postmarketing Experience

The following events have been reported during postapproval use of carisoprodol. Because these reactions are reported voluntarily from a population of uncertain size, it is not always possible to reliably estimate their frequency or establish a causal relationship to drug exposure.

Cardiovascular: Tachycardia, postural hypotension, and facial flushing [see OVERDOSAGE (10)].
Central Nervous System: Drowsiness, dizziness, vertigo, ataxia, tremor, agitation, irritability, headache, depressive reactions, syncope, insomnia, and seizures [see OVERDOSAGE (10)].
Gastrointestinal: Nausea, vomiting, and epigastric discomfort.
Hematologic: Leukopenia, pancytopenia

DRUG INTERACTIONS

7.1 CNS Depressants

The sedative effects of carisoprodol and other CNS depressants (e.g., alcohol, benzodiazepines, opioids, tricyclic antidepressants) may be additive. Therefore, caution should be exercised with patients who take more than one of these CNS depressants simultaneously. Concomitant use of carisoprodol and meprobamate, a metabolite of carisoprodol, is not recommended [see WARNINGS AND PRECAUTIONS (5.1)].

7.2 CYP2C19 Inhibitors and Inducers

Carisoprodol is metabolized in the liver by CYP2C19 to form meprobamate [see CLINICAL PHARMACOLOGY (12.3)]. Co-administration of CYP2C19 inhibitors, such as omeprazole or fluvoxamine, with carisoprodol could result in increased exposure of carisoprodol and decreased exposure of meprobamate. Co-administration of CYP2C19 inducers, such as rifampin or St. John’s Wort, with carisoprodol could result in decreased exposure of carisoprodol and increased exposure of meprobamate. Low dose aspirin also showed an induction effect on CYP2C19. The full pharmacological impact of these potential alterations of exposures in terms of either efficacy or safety of carisoprodol is unknown.

USE IN SPECIFIC POPULATIONS

8.1 Pregnancy

Risk Summary
Data over many decades of carisoprodol use in pregnancy have not identified a drug-associated risk of major birth defects, miscarriage, or other adverse maternal or fetal outcomes. Data on meprobamate, the primary metabolite of carisoprodol, also do not show a consistent association between maternal use of meprobamate and an increased risk of major birth defects (see DATA).

In a published animal reproduction study, pregnant mice administered carisoprodol orally at 2.6 and 4.1-times the maximum recommended human dose ([MRHD] of 1400 mg per day [350 mg QID] based on body surface area [BSA] comparison) from gestation through weaning resulted in reduced fetal weights, postnatal weight gain, and postnatal survival (see DATA)..

The estimated background risk of major birth defects and miscarriage for the indicated population is unknown. All pregnancies have a background risk of birth defect, loss, or other adverse outcomes. In the U.S. general population, the estimated background risk of major birth defects and miscarriage in clinically recognized pregnancies is 2 to 4% and 15 to 20%, respectively.

Data
Human Data
Retrospective case-control and cohort studies of meprobamate use during the first trimester of pregnancy have not consistently identified an increased risk or pattern of major birth defects. For children exposed to meprobamate in-utero, one study found no adverse effect on mental or motor development or IQ scores.

Animal Data
Embryofetal development studies in animals have not been completed.

In a published pre- and post-natal development animal study, pregnant mice administered carisoprodol orally at 300, 750, or 1200 mg/kg/day (approximately 1-, 2.6-, and 4.1-times the MRHD based on BSA comparison) from 7-days prior to gestation through birth and from lactation through weaning resulted in reduced fetal weights, postnatal weight gain, and postnatal survival at 2.6- and 4.1-times the MRHD.

8.2 Lactation

Risk Summary
Data from published literature report that carisoprodol and its metabolite, meprobamate, are present in breastmilk. There are no data on the effect of carisoprodol on milk production. There is one report of sedation in an infant who was breastfed by a mother taking carisoprodol (see CLINICAL CONSIDERATIONS). Because there have been no consistent reports of adverse events in breastfed infants over decades of use, the developmental and health benefits of breastfeeding should be considered along with the mother’s clinical need for carisoprodol and any potential adverse effects on the breastfed infant from carisoprodol or from the underlying maternal condition.

Clinical Considerations
Infants exposed to carisoprodol through breast milk should be monitored for sedation.

8.4 Pediatric Use

The efficacy, safety, and pharmacokinetics of carisoprodol in pediatric patients less than 16 years of age have not been established.

8.5 Geriatric Use

The efficacy, safety, and pharmacokinetics of carisoprodol in patients over 65 years old have not been established.

8.6 Renal Impairment

The safety and pharmacokinetics of carisoprodol in patients with renal impairment have not been evaluated. Since carisoprodol is excreted by the kidney, caution should be exercised if carisoprodol is administered to patients with impaired renal function. Carisoprodol is dialyzable by hemodialysis and peritoneal dialysis.

8.7 Hepatic Impairment

The safety and pharmacokinetics of carisoprodol in patients with hepatic impairment have not been evaluated. Since carisoprodol is metabolized in the liver, caution should be exercised if carisoprodol is administered to patients with impaired hepatic function.

8.8 Patients with Reduced CYP2C19 Activity

Patients with reduced CYP2C19 activity have higher exposure to carisoprodol. Therefore, caution should be exercised in administration of carisoprodol to these patients. [see CLINICAL PHARMACOLOGY (12.3)].

DRUG ABUSE AND DEPENDENCE

9.1 Controlled Substance

Carisoprodol is a Schedule IV controlled substance. Carisoprodol has been subject to abuse, misuse, and criminal diversion for nontherapeutic use [see WARNINGS AND PRECAUTIONS (5.2)].

9.2 Abuse

Abuse of carisoprodol poses a risk of overdosage which may lead to death, CNS and respiratory depression, hypotension, seizures and other disorders [see WARNINGS AND PRECAUTIONS (5.2) and OVERDOSAGE (10)]. Patients at high risk of carisoprodol abuse may include those with prolonged use of carisoprodol, with a history of drug abuse, or those who use carisoprodol in combination with other abused drugs.

Prescription drug abuse is the intentional non-therapeutic use of a drug, even once, for its rewarding psychological effects. Drug addiction, which develops after repeated drug abuse, is characterized by a strong desire to take a drug despite harmful consequences, difficulty in controlling its use, giving a higher priority to drug use than to obligations, increased tolerance, and sometimes physical withdrawal. Drug abuse and drug addiction are separate and distinct from physical dependence and tolerance (for example, abuse or addiction may not be accompanied by tolerance or physical dependence) [see DRUG ABUSE AND DEPENDENCE (9.3)].

9.3 Dependence

Tolerance is when a patient’s reaction to a specific dosage and concentration is progressively reduced in the absence of disease progression, requiring an increase in the dosage to maintain the same. Physical dependence is characterized by withdrawal symptoms after abrupt discontinuation or a significant dose reduction of a drug. Both tolerance and physical dependence have been reported with the prolonged use of carisoprodol. Reported withdrawal symptoms with carisoprodol include insomnia, vomiting, abdominal cramps, headache, tremors, muscle twitching, anxiety, ataxia, hallucinations, and psychosis. Instruct patients taking large doses of carisoprodol or those taking the drug for a prolonged time to not abruptly stop carisoprodol [see WARNINGS AND PRECAUTIONS (5.2)].

OVERDOSAGE

Clinical Presentation
Overdosage of carisoprodol commonly produces CNS depression. Death, coma, respiratory depression, hypotension, seizures, delirium, hallucinations, dystonic reactions, nystagmus, blurred vision, mydriasis, euphoria, muscular incoordination, rigidity, and/or headache have been reported with carisoprodol overdosage. Serotonin syndrome has been reported with carisoprodol intoxication. Many of the carisoprodol overdoses have occurred in the setting of multiple drug overdoses (including drugs of abuse, illegal drugs, and alcohol). The effects of an overdose of carisoprodol and other CNS depressants (e.g., alcohol, benzodiazepines, opioids, tricyclic antidepressants) can be additive even when one of the drugs has been taken in the recommended dosage. Fatal accidental and non-accidental overdoses of carisoprodol have been reported alone or in combination with CNS depressants.

Treatment of Overdosage
Basic life support measures should be instituted as dictated by the clinical presentation of the carisoprodol overdose. Vomiting should not be induced because of the risk of CNS and respiratory depression, and subsequent aspiration. Circulatory support should be administered with volume infusion and vasopressor agents if needed. Seizures should be treated with intravenous benzodiazepines and the reoccurrence of seizures may be treated with phenobarbital. In cases of severe CNS depression, airway protective reflexes may be compromised and tracheal intubation should be considered for airway protection and respiratory support.

For decontamination in cases of severe toxicity, activated charcoal should be considered in a hospital setting in patients with large overdoses who present early and are not demonstrating CNS depression and can protect their airway.

For more information on the management of an overdose of carisoprodol, contact a Poison Control Center.

DESCRIPTION

Carisoprodol tablets are available as 350 mg round, white tablets. Carisoprodol is a white, crystalline powder, having a mild, characteristic odor and a bitter taste. It is slightly soluble in water; freely soluble in alcohol, in chloroform, and in acetone; and its solubility is practically independent of pH. Carisoprodol is present as a racemic mixture.
Chemically, carisoprodol is (±)-2-Methyl-2-propyl-1,3-propanediol carbamate isopropylcarbamate and the molecular formula is C12H24N2O4, with a molecular weight of 260.33. The structural formula is:

[Structural Formula]

Other ingredients in the carisoprodol drug product include hydroxypropyl methylcellulose, lactose monohydrate, microcrystalline cellulose, sodium starch glycolate, stearic acid and talc.

HOW SUPPLIED

350 mg Tablets: round, convex, white tablets, inscribed with 111 on one side and “O” on the other side; available in bottles of 100 (NDC 69584-111-10), bottles of 500 (NDC 69584-111-50) and bottles of 1000 (NDC 69584-111-90).

Storage
Store at controlled room temperature 20° - 25°C (68° - 77°F).

PATIENT COUNSELING INFORMATION

Patients should be advised to contact their physician if they experience any adverse reactions to carisoprodol.

Sedation
Advise patients that carisoprodol may cause drowsiness and/or dizziness, and has been associated with motor vehicle accidents. Patients should be advised to avoid taking carisoprodol before engaging in potentially hazardous activities such as driving a motor vehicle or operating machinery [see WARNINGS AND PRECAUTIONS (5.1)].

Avoidance of Alcohol and Other CNS Depressants
Advise patients to avoid alcoholic beverages while taking carisoprodol and to check with their doctor before taking other CNS depressants such as benzodiazepines, opioids, tricyclic antidepressants, sedating antihistamines, or other sedatives [see WARNINGS AND PRECAUTIONS (5.1)].

Carisoprodol Should Only Be Used for Short-Term Treatment
Advise patients that treatment with carisoprodol should be limited to acute use (up to two or three weeks) for the relief of acute, musculoskeletal discomfort. In the post-marketing experience with carisoprodol, cases of dependence, withdrawal, and abuse have been reported with prolonged use. If the musculoskeletal symptoms still persist, patients should contact their healthcare provider for further evaluation.

Lactation
Advise nursing mothers using carisoprodol to monitor neonates for signs of sedation [see USE IN SPECIFIC POPULATIONS (8.2)].

Oxford Pharmaceuticals, LLC
Birmingham, AL 35211
8200005
09/2019 REV00
© 2019 Oxford Pharmaceuticals, LLC

PATIENT COUNSELING INFORMATION

Patients should be advised to contact their physician if they experience any adverse reactions to carisoprodol.

Sedation
Advise patients that carisoprodol may cause drowsiness and/or dizziness, and has been associated with motor vehicle accidents. Patients should be advised to avoid taking carisoprodol before engaging in potentially hazardous activities such as driving a motor vehicle or operating machinery [see WARNINGS AND PRECAUTIONS (5.1)].

Avoidance of Alcohol and Other CNS Depressants
Advise patients to avoid alcoholic beverages while taking carisoprodol and to check with their doctor before taking other CNS depressants such as benzodiazepines, opioids, tricyclic antidepressants, sedating antihistamines, or other sedatives [see WARNINGS AND PRECAUTIONS (5.1)].

Carisoprodol Should Only Be Used for Short-Term Treatment
Advise patients that treatment with carisoprodol should be limited to acute use (up to two or three weeks) for the relief of acute, musculoskeletal discomfort. In the post-marketing experience with carisoprodol, cases of dependence, withdrawal, and abuse have been reported with prolonged use. If the musculoskeletal symptoms still persist, patients should contact their healthcare provider for further evaluation.

Lactation
Advise nursing mothers using carisoprodol to monitor neonates for signs of sedation [see USE IN SPECIFIC POPULATIONS (8.2)].

Oxford Pharmaceuticals, LLC
Birmingham, AL 35211
8200005
09/2019 REV00
© 2019 Oxford Pharmaceuticals, LLC